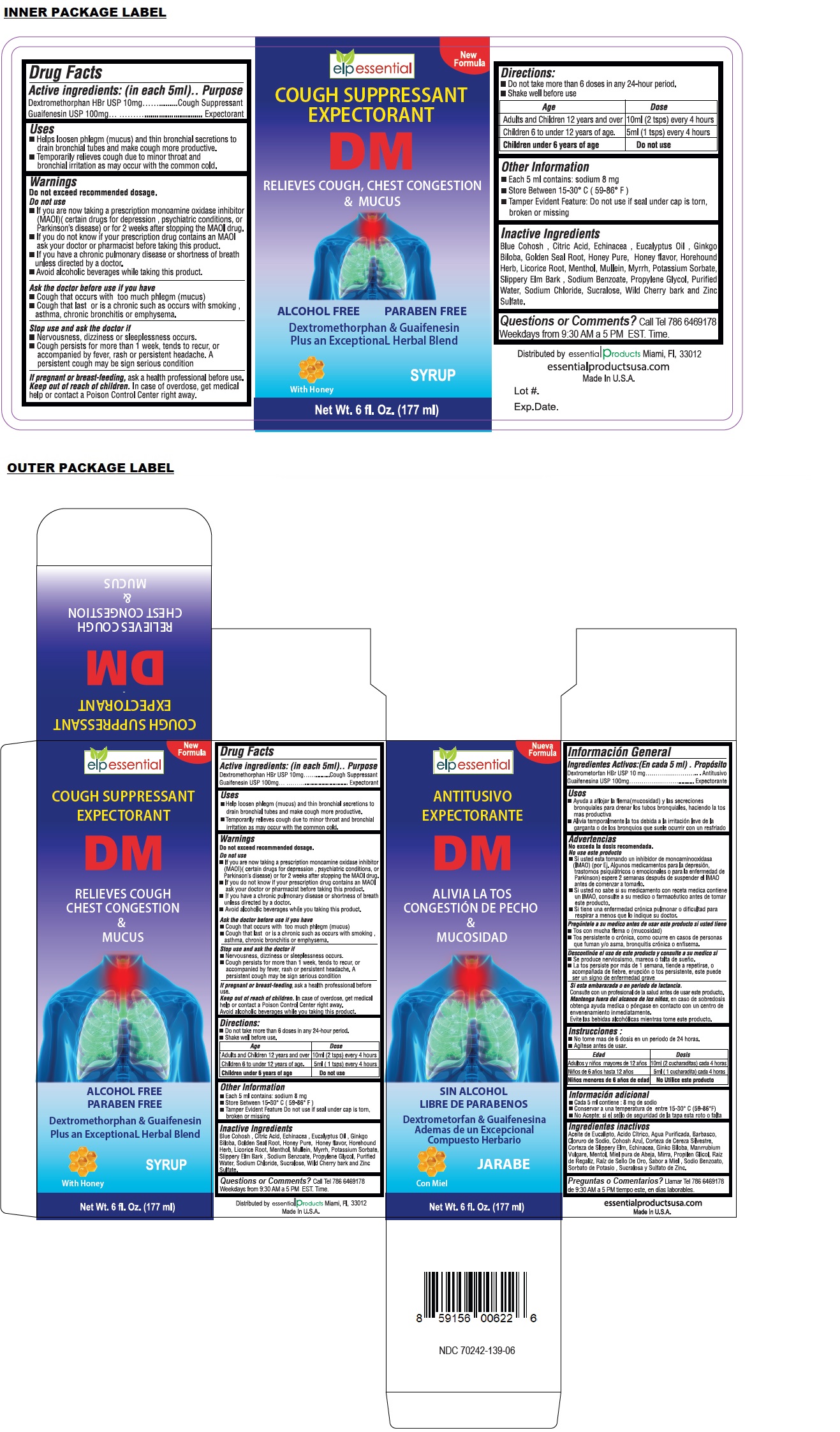 DRUG LABEL: elp essential DM
NDC: 70242-139 | Form: SYRUP
Manufacturer: Dannso Corp./d.b.a. Essential Products
Category: otc | Type: HUMAN OTC DRUG LABEL
Date: 20231027

ACTIVE INGREDIENTS: DEXTROMETHORPHAN HYDROBROMIDE 10 mg/5 mL; GUAIFENESIN 100 mg/5 mL
INACTIVE INGREDIENTS: CAULOPHYLLUM THALICTROIDES ROOT; CITRIC ACID MONOHYDRATE; ECHINACEA, UNSPECIFIED; EUCALYPTUS OIL; GINKGO; GOLDENSEAL; HONEY; HOREHOUND; LICORICE; MENTHOL, UNSPECIFIED FORM; VERBASCUM THAPSUS WHOLE; MYRRH; POTASSIUM SORBATE; ULMUS RUBRA BARK; SODIUM BENZOATE; PROPYLENE GLYCOL; WATER; SODIUM CHLORIDE; SUCRALOSE; PRUNUS SEROTINA BARK; ZINC SULFATE, UNSPECIFIED FORM

elp essential DM

Active ingredients: (in each 5 ml)

Dextromethorphan HBr USP 10mg
Guaifenesin USP 100mg

Purpose

Cough Suppressant
Expectorant

Uses

• Help loosen phlegm (mucus) and thin bronchial secretions to drain bronchial tubes and make cough more productive.
• Temporarily relieves cough due to minor throat and bronchial irritation as may occur with the common cold.

Warnings

Do not exceed recommended dosage.

Do not use
• If you are now taking a prescription monoamine oxidase inhibitor (MAOI) (certain drugs for depression, psychiatric conditions, or Parkinson's disease) or for 2 weeks after stopping the MAOI drug.
• If you do not know if your prescription drug contains an MAOI ask your doctor or pharmacist before taking this product.
• If you have a chronic pulmonary disease or shortness of breath unless directed by a doctor.
• Avoid alcoholic beverages while you taking this product.

Ask the doctor before use if you have
• Cough that occurs with too much phlegm (mucus)
• Cough that last or is a chronic such as occurs with smoking, asthma, chronic bronchitis or emphysema.

Stop use and ask the doctor if
• Nervousness, dizziness or sleeplessness occurs.
• Cough persists for more than 1 week, tends to recur, or accompanied by fever, rash or persistent headache. A persistent cough may be sign serious condition

If pregnant or breast-feeding, ask a health professional before use.

Keep out of reach of children. In case of overdose, get medical help or contact a Poison Control Center right away.

Directions:

• Do not take more than 6 doses in any 24-hour period.
• Shake well before use.

Age | Dose
Adults and Children 12 years and over | 10ml (2 tsps) every 4 hours
Children 6 to under 12 years of age. | 5ml (1 tsps) every 4 hours
Children under 6 years of age | Do not use

Other Information

• Each 5 ml contains: sodium 8 mg
• Store Between 15-30° C (59-86° F)
• Tamper Evident Feature Do not use if seal under cap is torn, broken or missing

Inactive Ingredients

Blue Cohosh, Citric Acid, Echinacea, Eucalyptus Oil, Ginkgo Biloba, Golden Seal Root, Honey Pure, Honey flavor, Horehound Herb, Licorice Root, Menthol, Mullein, Myrrh, Potassium Sorbate, Slippery Elm Bark, Sodium Benzoate, Propylene Glycol, Purified Water, Sodium Chloride, Sucralose, Wild Cherry bark and Zinc Sulfate.

Questions or Comments?

Call Tel 786 6469178
Weekdays from 9:30 AM to 5 PM EST. Time.

New Formula

RELIEVES COUGH CHEST CONGESTION & MUCUS

ALCOHOL FREE

PARABEN FREE

Dextromethorphan & Guaifenesin Plus an ExceptionaL Herbal Blend

With Honey

Distributed by essential products Miami, FI, 33012
Made In U.S.A.

essentialproductsusa.com